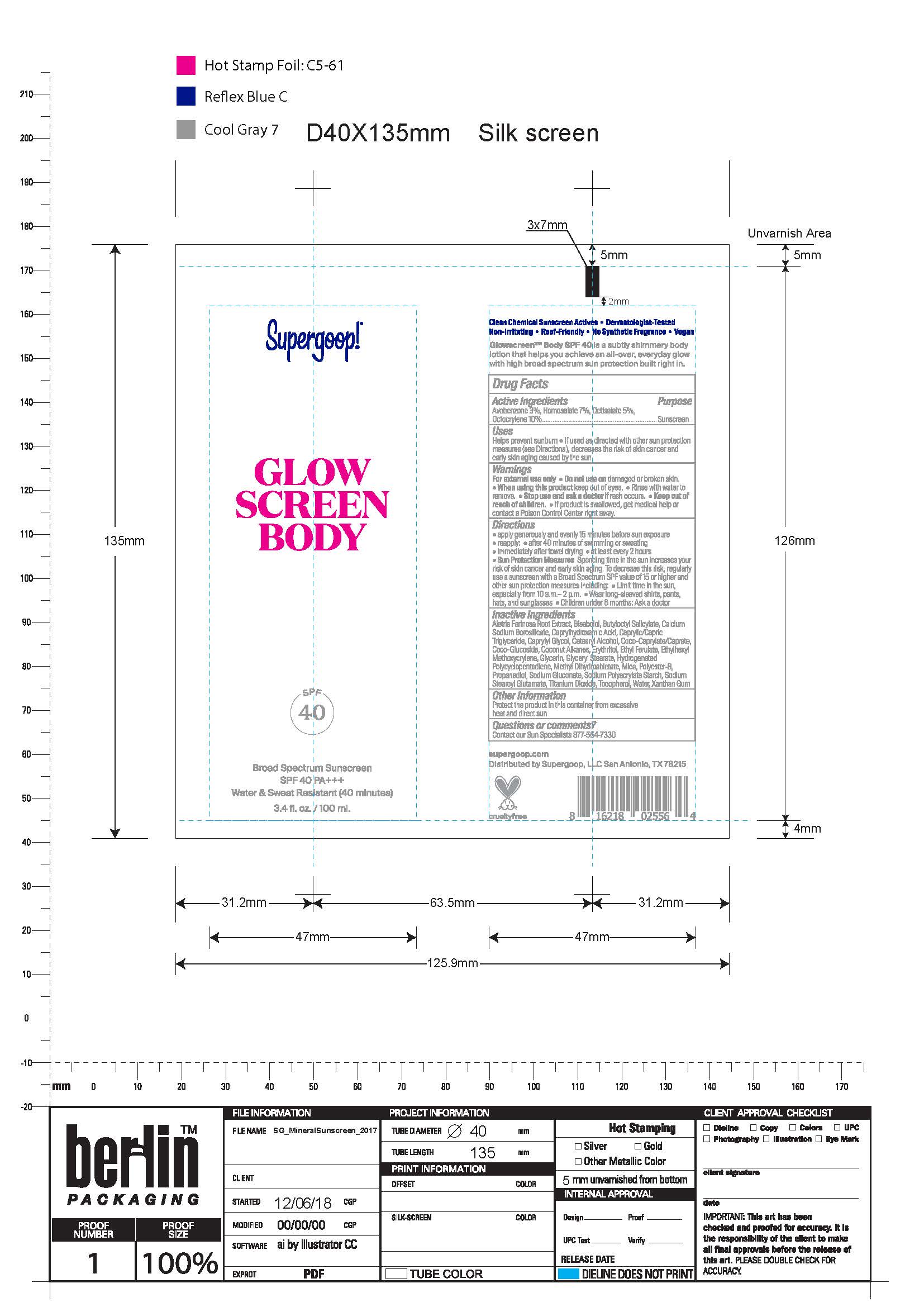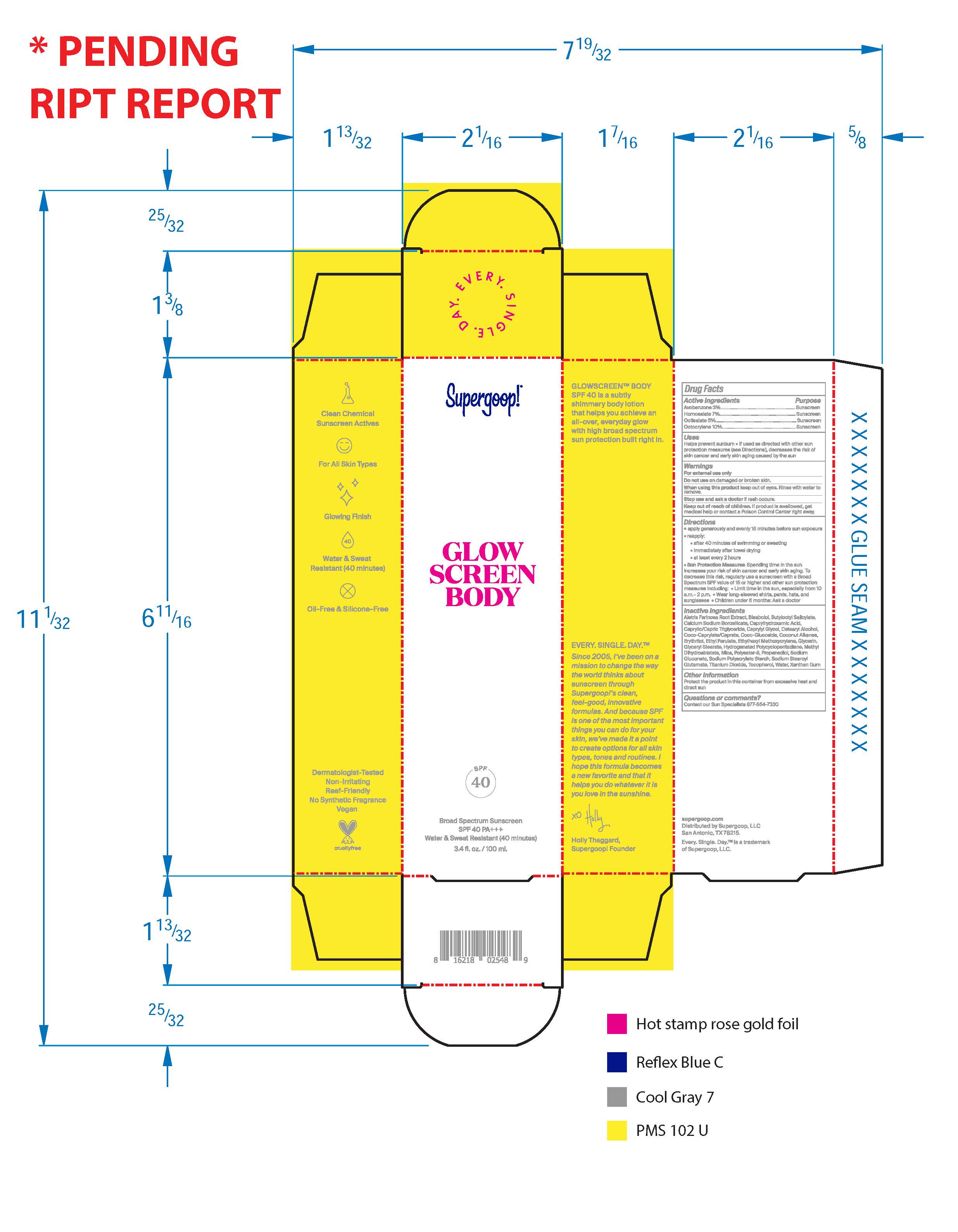 DRUG LABEL: Glow Screen Body Broad Spectrum Sunscreen SPF 40
NDC: 75936-350 | Form: CREAM
Manufacturer: Supergoop, LLC
Category: otc | Type: HUMAN OTC DRUG LABEL
Date: 20241204

ACTIVE INGREDIENTS: HOMOSALATE 7 g/100 mL; OCTISALATE 5 g/100 mL; OCTOCRYLENE 10 g/100 mL; AVOBENZONE 3 g/100 mL
INACTIVE INGREDIENTS: CAPRYLHYDROXAMIC ACID; MEDIUM-CHAIN TRIGLYCERIDES; PROPANEDIOL; WATER; ERYTHRITOL; ETHYL FERULATE; CETOSTEARYL ALCOHOL; ALETRIS FARINOSA ROOT; LEVOMENOL; BUTYLOCTYL SALICYLATE; TITANIUM DIOXIDE; COCO GLUCOSIDE; COCONUT ALKANES; ETHYLHEXYL METHOXYCRYLENE; GLYCERIN; CAPRYLYL GLYCOL; COCO-CAPRYLATE/CAPRATE; GLYCERYL MONOSTEARATE; MICA; SODIUM GLUCONATE; SODIUM STEAROYL GLUTAMATE; TOCOPHEROL; POLYESTER-8 (1400 MW, CYANODIPHENYLPROPENOYL CAPPED); XANTHAN GUM; METHYL DIHYDROABIETATE

Glow Screen Body Broad Spectrum Sunscreen SPF 40

ACTIVE INGREDIENT

Avobenzone 3%..............Sunscreen

Homosalate 7%.............Sunscreen

Octisalate 5%..................Sunscreen

Octocrylene 10%............Sunscreen

PURPOSE

- Helps prevent sunburn
- If used as directed with other sun protection measures (see Directions), decreases the risk of skin cancer and early skin aging caused by the sun.

Keep out of reach of children. If product is swallowed, get medical help or contact a Poison Control Center right away.

Stop use and ask a doctor if rash occurs.

WARNINGS

For external use only

Do not use on damaged or broken skin.

When using this product keep out of eyes. Rinse with water to remove.

DOSAGE AND ADMINISTRATION

- apply generously and evenly 15 minutes before sun exposure
- reapply:
- after 40 minutes of swimming or sweating
- immediately after towel drying
- at least every 2 hours
- Sun Protection Measures Spending time in the sun increases your risk of skin cancer and early skin aging. To decreases this risk, regularly use a sunscreen with a Broad Spectrum SPF value of 15 or higher and other sun protection meausres including: Limit time in the sun, especially from 10 a.m.-2 p.m. Wear long-sleeved shirts, pants, hats, and sunglassess. Children under 6 months: Ask a doctor.

INACTIVE INGREDIENT

Aletris Farinosa Root Extract, Bisabolol, Butyloctyl Salicylate,Calcium Sodium Borosilicate, Caprylhydroxamic Acid, Caprylic/Capric Triglyceride, Capryly Glycol, Cetearyl Alcohol, Coco-Caprylate/Caprate, Coco-Glucoside, Coconut Alkanes, Erythritol, Ethyl Ferulate, Ethylhexyl Methoxycrylene, Glycerin, Glyceryl Stearate, Hydrogenated Polycyclopentadiene, Methyl Dlhydroabietate, Mica, Polyester-8, Propanedlol, Sodium Gluconate, Sodium Polyacrylate Starch, Sodium Stearoyl Glutamate, Titanium Dioxide, Tocopherol, Water, Xanthan Gum

OTHER SAFETY INFORMATION

Protect the product in this container from excessive heat and direct sun

PACKAGE LABEL

Supergoop!

Glow Screen Body

SPF 40

Broad Spectrum Sunscreen

SPF 40 PA+++

Water & Sweat Resistant (40 minutes)

3.4 fl. oz. / 100 ml.